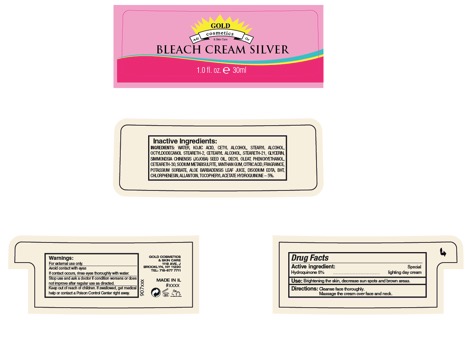 DRUG LABEL: Gold Cosmetics Bleach Cream Silver
NDC: 69435-1801 | Form: CREAM
Manufacturer: Peer Pharm Ltd
Category: otc | Type: HUMAN OTC DRUG LABEL
Date: 20180509

ACTIVE INGREDIENTS: HYDROQUINONE 5 mg/100 mg
INACTIVE INGREDIENTS: GLYCERIN; JOJOBA OIL; DECYL OLEATE; SODIUM METABISULFITE; XANTHAN GUM; PHENOXYETHANOL; CITRIC ACID MONOHYDRATE; POTASSIUM SORBATE; ALOE VERA LEAF; BUTYLATED HYDROXYTOLUENE; WATER; CETOSTEARYL ALCOHOL; STEARYL ALCOHOL; CETEARETH-30; STEARETH-21; STEARETH-2; EDETATE DISODIUM ANHYDROUS; CHLORPHENESIN; CETYL ALCOHOL; ALLANTOIN; ALPHA-TOCOPHEROL ACETATE; KOJIC ACID; OCTYLDODECANOL

Bleach Cream Silver

ACTIVE INGREDIENT

Hydroquinone 5%

PURPOSE

Face cream for gradual fading of dark spots

INDICATIONS AND USAGE

Face cream for gradual fading of dark spots

Apply a very thin layer once a day, only at night, all over the face

DOSAGE AND ADMINISTRATION

Apply a very thin layer once a day, only at night, all over the face

Warnings:

- For external use only
- Avoid contact with eyes
- If contact occurs, rinse eyes thoroughly with water

Keep out of reach of children